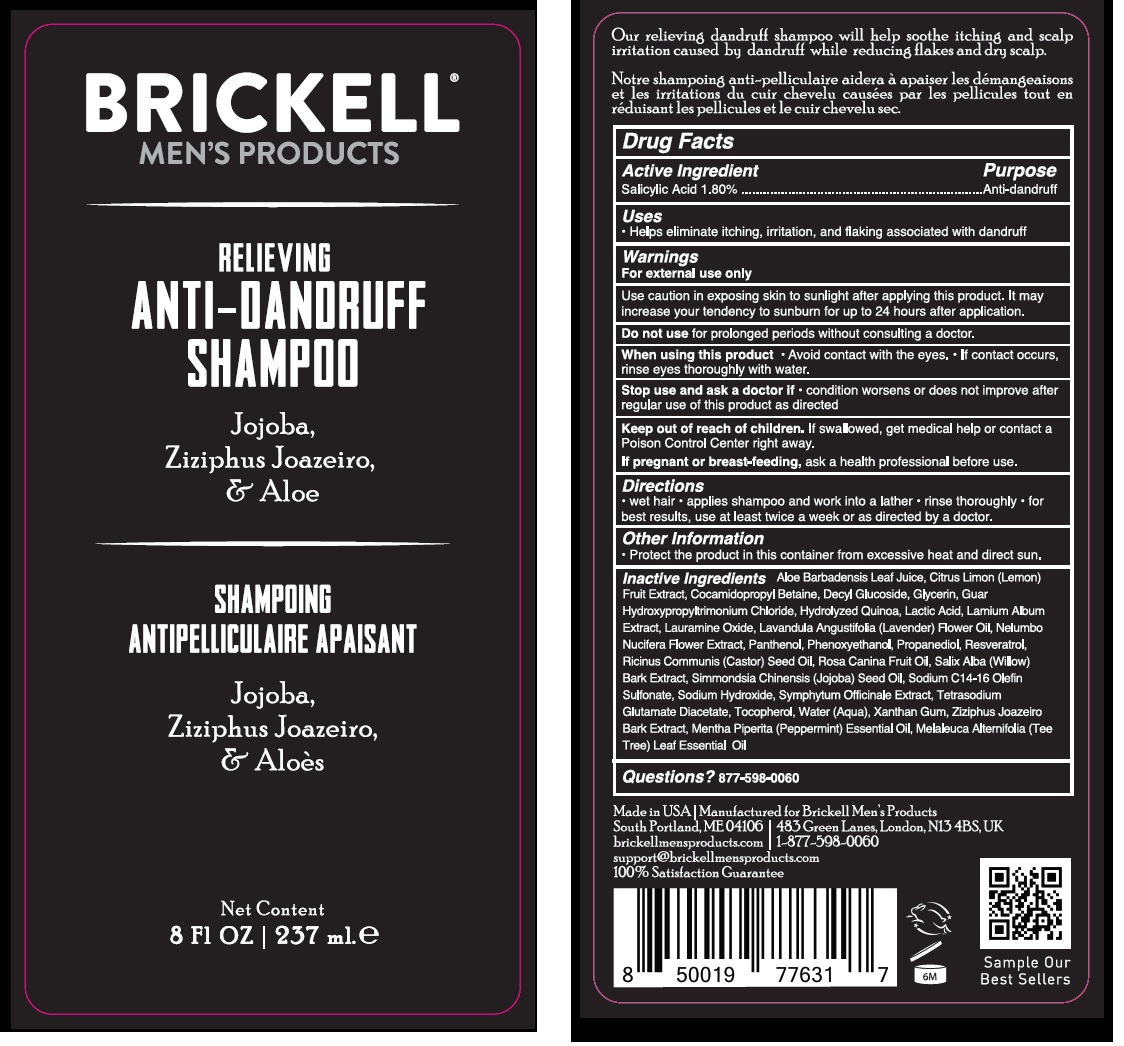 DRUG LABEL: Brickell Mens Products Relieving Anti-Dandruff
NDC: 82247-617 | Form: LIQUID
Manufacturer: BRICKELL BRANDS LLC
Category: otc | Type: HUMAN OTC DRUG LABEL
Date: 20250616

ACTIVE INGREDIENTS: SALICYLIC ACID 18 mg/1 mL
INACTIVE INGREDIENTS: ALOE VERA LEAF JUICE; LEMON BALM OIL; COCAMIDOPROPYL BETAINE; DECYL GLUCOSIDE; GLYCERIN; GUAR HYDROXYPROPYLTRIMONIUM CHLORIDE; LACTIC ACID, UNSPECIFIED FORM; LAMIUM ALBUM WHOLE; LAURAMINE OXIDE; NELUMBO NUCIFERA FLOWER; PANTHENOL; PHENOXYETHANOL; PROPANEDIOL; RESVERATROL; CASTOR OIL; ROSA CANINA FRUIT OIL; SALIX ALBA BARK; JOJOBA OIL; SODIUM C14-16 OLEFIN SULFONATE; SODIUM HYDROXIDE; TETRASODIUM GLUTAMATE DIACETATE; TOCOPHEROL; WATER; XANTHAN GUM; SARCOMPHALUS JOAZEIRO BARK; PEPPERMINT; MELALEUCA ALTERNIFOLIA LEAF

Brickell Men's Products Relieving Anti-Dandruff Shampoo

Active Ingredient

Salicylic Acid 1.80%

Purpose

Anti-dandruff

Uses

- Helps eliminate itching, irritation, and flaking associated with dandruff

Warnings

For external use only

Use caution in exposing skin to sunlight after applying this product. It may increase your tendency to sunburn for up to 24 hours after application.

Do not use

for prolonged periods without consulting a doctor.

When using this product

- Avoid contact with the eyes.
- If contact occurs, rinse eyes thoroughly with water.

Stop use and ask a doctor if

- condition worsens or does not improve after regular use of this product as directed

Keep out of reach of children.

If swallowed, get medical help or contact a Poison Control Center right away.

If pregnant or breast-feeding,

ask a health professional before use.

Directions

- wet hair
- applies shampoo and work into a lather
- rinse thoroughly
- for best results, use at least twice a week or as directed by a doctor.

Other Information

- Protect the product in this container from excessive heat and direct sun.

Inactive Ingredients

Aloe Barbadensis Leaf Juice, Citrus Limon (Lemon) Fruit Extract, Cocamidopropyl Betaine, Decyl Glucoside, Glycerin, Guar Hydroxypropyltrimonium Chloride, Hydrolyzed Quinoa, Lactic Acid, Lamium Album Extract, Lauramine Oxide, Lavandula Angustifolia (Lavender) Flower Oil, Nelumbo Nucifera Flower Extract, Panthenol, Phenoxyethanol, Propanediol, Resveratrol, Ricinus Communis (Castor) Seed Oil, Rosa Canina Fruit Oil, Salix Alba (Willow) Bark Extract, Simmondsia Chinensis (Jojoba) Seed Oil, Sodium C14-16 Olefin Sulfonate, Sodium Hydroxide, Symphytum Officinale Extract, Tetrasodium Glutamate Diacetate, Tocopherol, Water (Aqua), Xanthan Gum, Ziziphus Joazeiro Bark Extract, Mentha Piperita (Peppermint) Essential Oil, Melaleuca Alternifolia (Tee Tree) Leaf Essential Oil

Questions?

877-598-0060